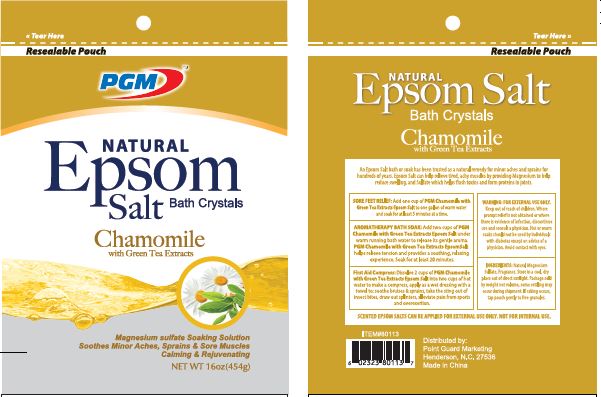 DRUG LABEL: Green Tea Chamomile Natural Epsom Salt
NDC: 69232-004 | Form: POWDER
Manufacturer: Anhui Twowin Machinery Imp. & Exp. Co., Ltd.
Category: otc | Type: HUMAN OTC DRUG LABEL
Date: 20160210

ACTIVE INGREDIENTS: MAGNESIUM SULFATE 10 g/10 g
INACTIVE INGREDIENTS: CHAMOMILE; GREEN TEA LEAF

Active Ingredient ..................................................................... Purpose

Magnesium Sulfate USP (Epsom Salt)

Internal Use ....................................................................... Saline Laxative

External Use .................................................................... Soaking Solution

PURPOSE

Uses (Internal)

- Relieves occasional constipation (irregularity)
- Generally produces bowel movements in 1/2 to 6 hours

Uses (External)

- Relieves pain from minor sprains and bruises

KEEP OUT OF REACH OF CHILDREN

Keep this and all drugs out of the reach of children. In case of accidental overdose, seek professional assistance or contact a Poison Control Center immediately.

DOSAGE AND ADMINISTRATION

Directions - For Internal Use as a Laxative

- do not exceed more than 2 doses per day
- may be taken as a single daily dose or in divided doses
- dissolve each dose in a full (8 ounces) of liquid

Age | Dose
adults and children 12 years and older | 2 to 4 level teaspoons (10 to 20 grams) daily
children 6 to under 12 years | 1 to 2 level teaspoons (5 to 10 grams) daily

Not recommended for children under 6 years of age.

INDICATIONS AND USAGE

Natural Epsom Salt

Magnesium Sulfate U.S.P.

Soaking Solution

Saline Laxative

Soothes Minor Aches, Sprains & Sore Muscles

Calming & Rejuvenating

SORE FEET RELIEF: Add one cup of Amoray Care® Epsom Salt to one gallon of warm water and soak for at least 5 minutes at a time.

BATH SOAK: Add two cups of Amoray Care® Epsom Salt under warm running bath water to release its gentle aroma. Amoray Care® Epsom Salt helps relieve tension and provides a soothing, relaxing experience. Soak for at least 20 minutes.

First Aid Compress: Dissolve 2 cups of Amoray Care® Epsom Salt into two cups of hot water to make a compress, apply as a wet dressing with a towel to: soothe bruises & sprains, take the sting out of insect bites, draw out splinters, alleviate pain from sports and overexertion.

Kkeep out of reach of children. Where prompt relief is not obtained or where there is evidence of infection, discontinue use and consult a physician. Hot or warm soaks should not be used by individuals with diabetes except on advice of a physician. Avoid contact with eyes.

EPSOM SALT WITHOUT SCENT CAN BE APPLIED FOR BOTH INTERNAL AND EXTERNAL USE, SCENTED EPSOM SALTS CAN BE APPLIED FOR EXTERNAL USE ONLY.

Store in a cool, dry place out of direct sunlight. Package sold by weight not volume, some settling may occur during shipment. If caking occurs, tap pouch gently to free granules.

WARNINGS

Warnings • Ask a doctor before use if you have:

Kidney disease

a magnesium restricted diet

abdominal pain, nausea or vomiting

noticed a sudden change in bowel habits that persists over a period of 2 weeks

already used a laxative for a period longer than 1 week

Ask a doctor or pharmacist before use if you are presently taking any other drug. Take this product 2 or more hours before or after other drugs. Laxatives may affect how other drugs work.

When using this product, do not use more than directed.

Stop and consult a doctor if:

As laxative: • you have rectal bleeding or fail to have a bowel movement after use. This may indicate a serious condition. • You need to use a laxative for more than 1 week

As soaking solution: • you have redness, irritation, swelling, or infection occurs • hot or warm soaks should not be used by individuals with diabetes except with the advice of a physician

If pregnant or breast-feeding, ask a health professional before use.

EPSOM SALT WITHOUT SCENT CAN BE APPLIED FOR BOTH INTERNAL AND EXTERNAL USE, SCENTED EPSOM SALTS CAN BE APPLIED FOR EXTERNAL USE ONLY.

INACTIVE INGREDIENT

Ingredients:

Natural Magnesium Sulfate